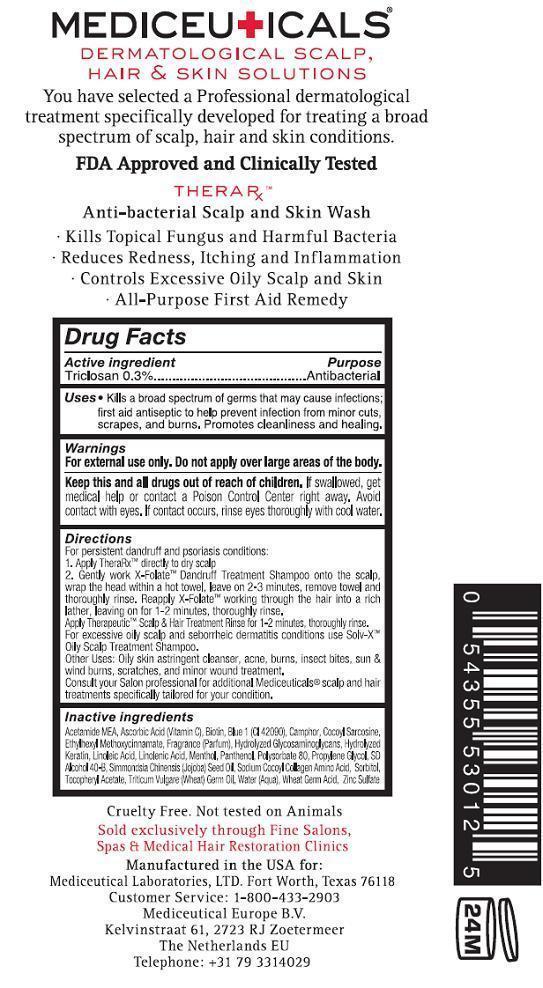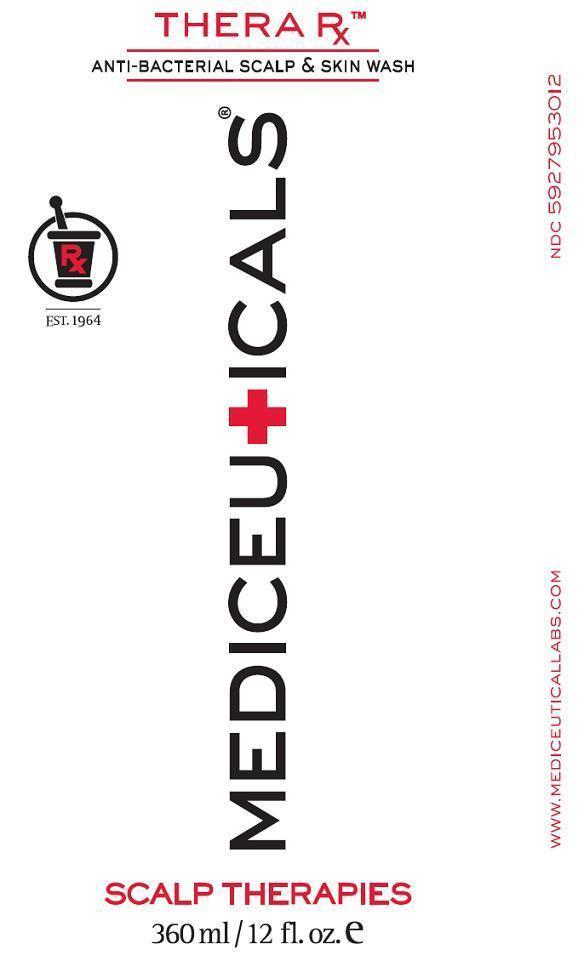 DRUG LABEL: THERA RX
NDC: 59279-530 | Form: SOLUTION
Manufacturer: Mediceutical Laboratories, LTD
Category: otc | Type: HUMAN OTC DRUG LABEL
Date: 20121001

ACTIVE INGREDIENTS: TRICLOSAN 3 mg/1 mL
INACTIVE INGREDIENTS: ACETIC MONOETHANOLAMIDE; ASCORBIC ACID; BIOTIN; FD&C BLUE NO. 1; CAMPHOR (SYNTHETIC); SARCOSINE; OCTINOXATE; LINOLEIC ACID; LINOLENIC ACID; MENTHOL; PANTHENOL; POLYSORBATE 80; PROPYLENE GLYCOL; ALCOHOL; JOJOBA OIL; SORBITOL; .ALPHA.-TOCOPHEROL ACETATE, D-; WHEAT GERM OIL; WATER; ZINC SULFATE

THERA Rx

Active ingredient

Triclosan 0.3%

Purpose

Antibacterial

Uses

- Kills a broad spectrum of germs that may cause infections; first aid antiseptic to help prevent infection from minor cuts, scrapes, and burns. Promotes cleanliness and healing.

Warnings

For external use only. Do not apply over large areas of the body.

Keep this and all drugs out of reach of children.

If swallowed, get medical help or contact a Poison Control Center right away. Avoid contact with eyes. If contact occurs, rinse eyes thoroughly with cool water.

Directions

For persistent dandruff and psoriasis conditions:

1. Apply Thera RxTM directly to dry scalp
2. Gently work X-FolateTM Dandruff Treatment Shampoo onto the scalp, wrap the head within a hot towel, leave on 2-3 minutes, remove towel and thoroughly rinse. Reapply X-FolateTM working through the hair into a rich lather, leaving on for 1-2 minutes, thoroughly rinse.

Apply TherapeuticTM Scalp and Hair Treatment Rinse for 1-2 minutes, thoroughly rinse.
For Excessive oily scalp and seborrheic dermatitis conditions use Solv-XTM Oily Scalp Treatment Shampoo.
Other Uses: Oily skin astringent cleanser, acne, burns, insect bites, sun and wind burns, scratches, and minor would treatment.
Consult your Salon professional for additional Mediceuticals® scalp and hair treatments specifically tailored for your condition.

Inactive ingredients

Acetamide MEA, Ascorbic Acid (Vitamin C) Biotin, Blue1 (CI 42090), Camphor, Cocoyl Sarcosine, Ethylhexyl Methoxycinnamate, Fragrance (Parfum), Hydrolyzed Glycosaminoglycans, Hydrolyzed Keratin, Linoleic Acid, Linolenic Acid, Methanol, Panthenol, Polysorbate 80, Propylene Glycol, SD Alcohol 40-B, Simmondsia Chimensis (Jojoba) Seed Oil, Sodium Cocoyl Collagen Amino Acid, Sorbitol, Tocopheryl Acetate, Triticum Vulgare (Wheat) Germ Oil, Water (Aqua), Wheat Germ Acid, Zinc Sulfate

Package Label-Principal Display Panel

THERA RxTM
ANTIBACTERIAL SCALP AND SKIN WASH

MEDICEUTICALS®
Cruelty Free. Not tested on Animals.
Sold exclusively through fine Salons, Spas and Hair Restoration Clinics

Manufactured in the USA for:

Mediceutical Laboratories, LTD Fort Worth, Texas 76118
Customer Service: 1-800-433-2903

Mediceutical Europe B.V.

Kelvinstraat 61, 2723 RJ Zoetermeer, The Netherlands EU

Telephone: +31 79 3314029

NDC 5927953006 THERA RxTM 6 fl oz

NDC 5927953012 THERA RxTM 12 fl oz

Front

Back